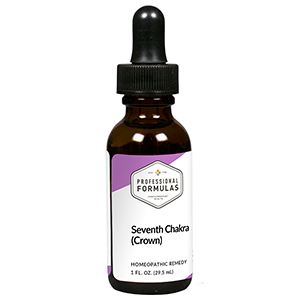 DRUG LABEL: Seventh Chakra (Crown)
NDC: 63083-7307 | Form: LIQUID
Manufacturer: Professional Complementary Health Formulas
Category: homeopathic | Type: HUMAN OTC DRUG LABEL
Date: 20190815

ACTIVE INGREDIENTS: AMARYLLIS BELLADONNA WHOLE 8 [hp_X]/29.5 mL; ANHYDROUS DIBASIC CALCIUM PHOSPHATE 8 [hp_X]/29.5 mL; CALCIUM SULFATE ANHYDROUS 8 [hp_X]/29.5 mL; SODIUM SULFATE 8 [hp_X]/29.5 mL; COLCHICUM AUTUMNALE BULB 12 [hp_X]/29.5 mL; FORMICA RUFA 12 [hp_X]/29.5 mL; NAJA NAJA VENOM 12 [hp_X]/29.5 mL; NERIUM OLEANDER WHOLE 12 [hp_X]/29.5 mL; CARBO ANIMALIS 15 [hp_X]/29.5 mL; CALCIUM FLUORIDE 30 [hp_X]/29.5 mL; CALCIUM CARBONATE 30 [hp_X]/29.5 mL
INACTIVE INGREDIENTS: ALCOHOL; WATER

RCT7

ACTIVE INGREDIENTS

Belladonna 8X
Calcarea phosphorica 8X
Calcarea sulphurica 8X
Natrum sulphuricum 8X
Colchicum autumnale 12X
Formica rufa 12X
Naja tripudians 12X
Oleander 12X
Carbo animalis 15X
Amethyst 30X, 60X, 100X
Calcite 30X, 60X, 100X

QUESTIONS

Professional Formulas

PO Box 2034 Lake Oswego, OR 97035

INDICATIONS

Temporarily relieves apathy, materialism, greed, boredom with life or difficulty finding meaning, constant worry, sadness, or general lack of purpose.*

PURPOSE

*Claims based on traditional homeopathic practice, not accepted medical evidence. Not FDA evaluated.

WARNINGS

In case of overdose, get medical help or contact a poison control center right away.

Keep out of the reach of children.

PREGNANCY OR BREAST FEEDING

If pregnant or breastfeeding, ask a healthcare professional before use.

DIRECTIONS

Place drops under tongue 30 minutes before/after meals. Adults and children 12 years and over: Take 5 drops up to 4 times per day for up to one month. Consult a physician for use in children under 12 years of age.

OTHER INFORMATION

Tamper resistant. If seal is broken, do not use. After opening, close container tightly and store at room temperature away from heat.

INACTIVE INGREDIENTS

20% ethanol, purified water.

LABEL

Est 1985

Professional Formulas

Complementary Health

Seventh Chakra (Crown)

Homeopathic Remedy

1 FL. OZ. (29.5 mL)